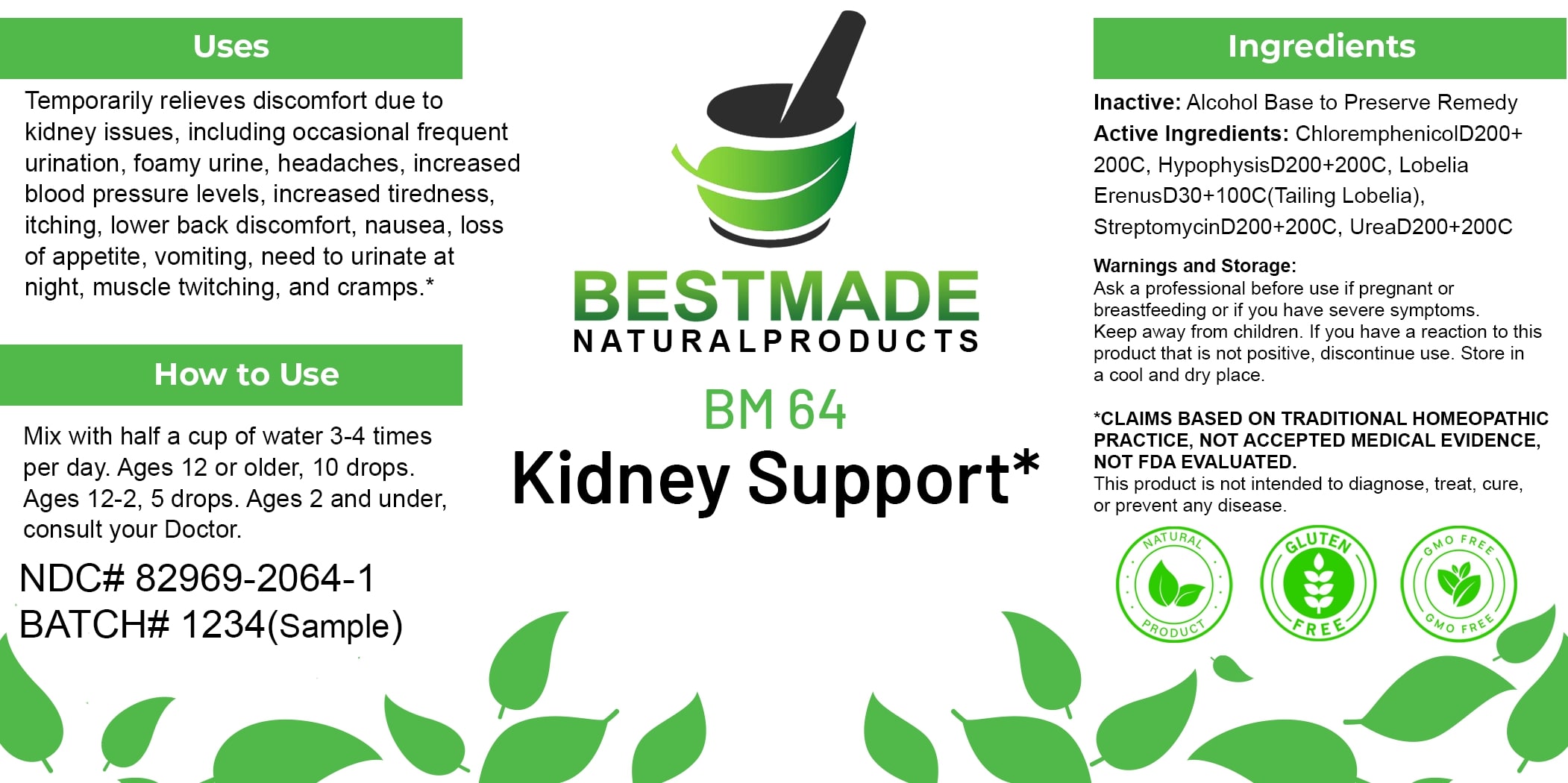 DRUG LABEL: Bestmade Natural Products BM64
NDC: 82969-2064 | Form: LIQUID
Manufacturer: Bestmade Natural Products
Category: homeopathic | Type: HUMAN OTC DRUG LABEL
Date: 20250130

ACTIVE INGREDIENTS: UREA 200 [hp_C]/200 [hp_C]; CHLORAMPHENICOL 200 [hp_C]/200 [hp_C]; LOBELIA ERINUS 200 [hp_C]/200 [hp_C]; STREPTOMYCES GRISEUS 200 [hp_C]/200 [hp_C]; SUS SCROFA PITUITARY GLAND 200 [hp_C]/200 [hp_C]
INACTIVE INGREDIENTS: ALCOHOL 200 [hp_C]/200 [hp_C]

BM64

DOSAGE AND ADMINISTRATION

How to Use

Mix with half a cup of water 3-4 times per day. Ages 12 or older, 10 drops. Ages 12-2, 5 drops. Ages 2 and under, consult your Doctor.

INACTIVE INGREDIENT

Ingredients

Inactive: Alcohol Base to Preserve Remedy

ACTIVE INGREDIENT

Active Ingredients: ChloremphenicolD200+200C, HypophysisD200+200C, Lobelia ErenusD30+100C(Tailing Lobelia), StreptomycinD200+200C, UreaD200+200C

Uses

Temporarily relieves discomfort due to kidney issues, including occasional frequent urination, foamy urine, headaches, increased blood pressure levels, increased tiredness, itching, lower back discomfort, nausea, loss of appetite, vomiting, need to urinate at night, muscle twitching, and cramps.*

*CLAIMS BASED ON TRADITIONAL HOMEOPATHIC PRACTICE, NOT ACCEPTED MEDICAL EVIDENCE, NOT FDA EVALUATED.

This product is not intended to diagnose, treat, cure, or prevent any disease.

Uses

Temporarily relieves discomfort due to kidney issues, including occasional frequent urination, foamy urine, headaches, increased blood pressure levels, increased tiredness, itching, lower back discomfort, nausea, loss of appetite, vomiting, need to urinate at night, muscle twitching, and cramps.*

*CLAIMS BASED ON TRADITIONAL HOMEOPATHIC PRACTICE, NOT ACCEPTED MEDICAL EVIDENCE, NOT FDA EVALUATED.

This product is not intended to diagnose, treat, cure, or prevent any disease.

KEEP OUT OF REACH OF CHILDREN

Warnings and Storage:

Ask a professional before use if pregnant or breastfeeding or if you have severe symptoms. Keep away from children. If you have a reaction to this product that is not positive, discontinue use. Store in a cool and dry place.

Warnings and Storage:

Ask a professional before use if pregnant or breastfeeding or if you have severe symptoms. Keep away from children. If you have a reaction to this product that is not positive, discontinue use. Store in a cool and dry place.

*CLAIMS BASED ON TRADITIONAL HOMEOPATHIC PRACTICE, NOT ACCEPTED MEDICAL EVIDENCE, NOT FDA EVALUATED.

This product is not intended to diagnose, treat, cure, or prevent any disease.

Entire package label